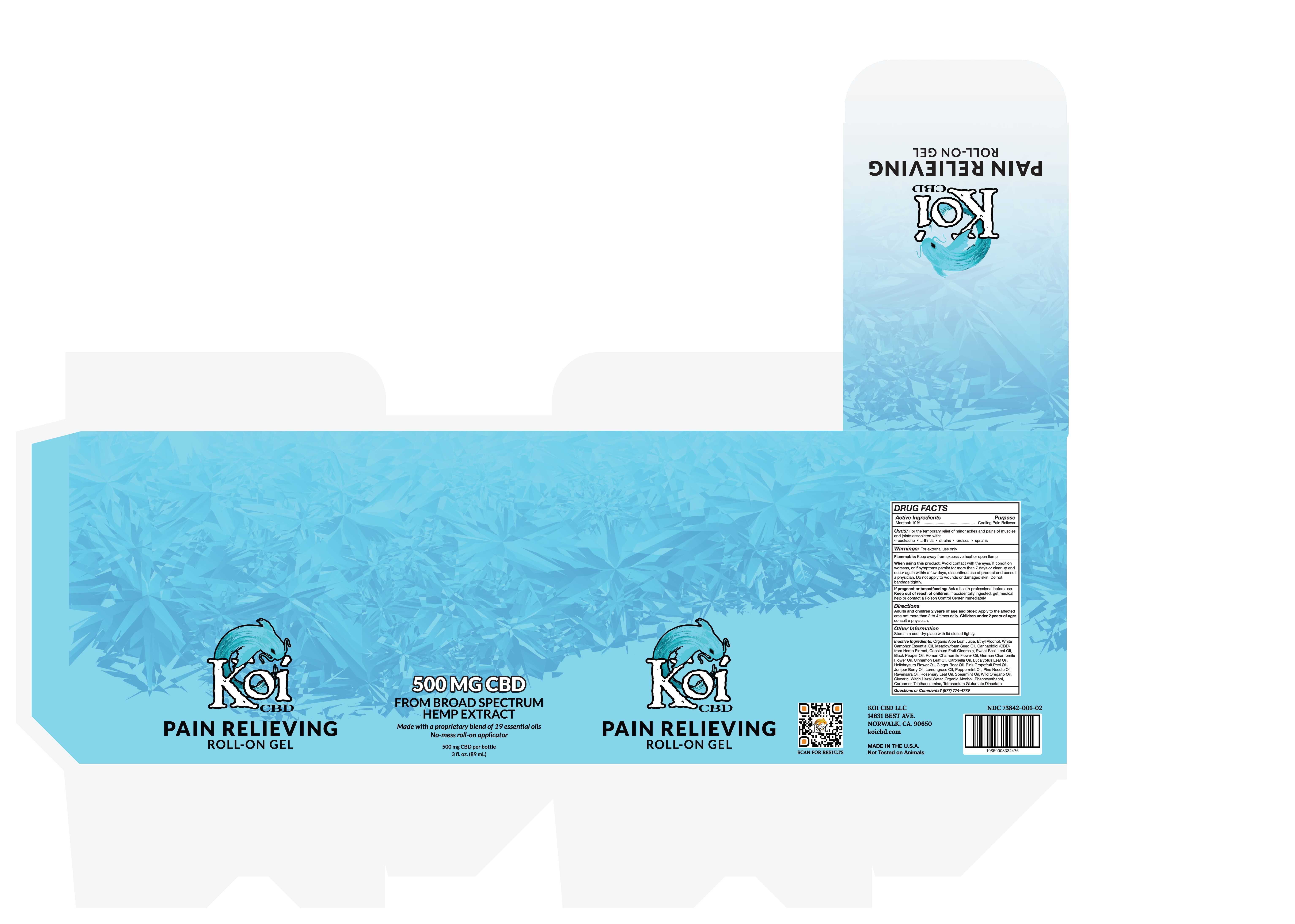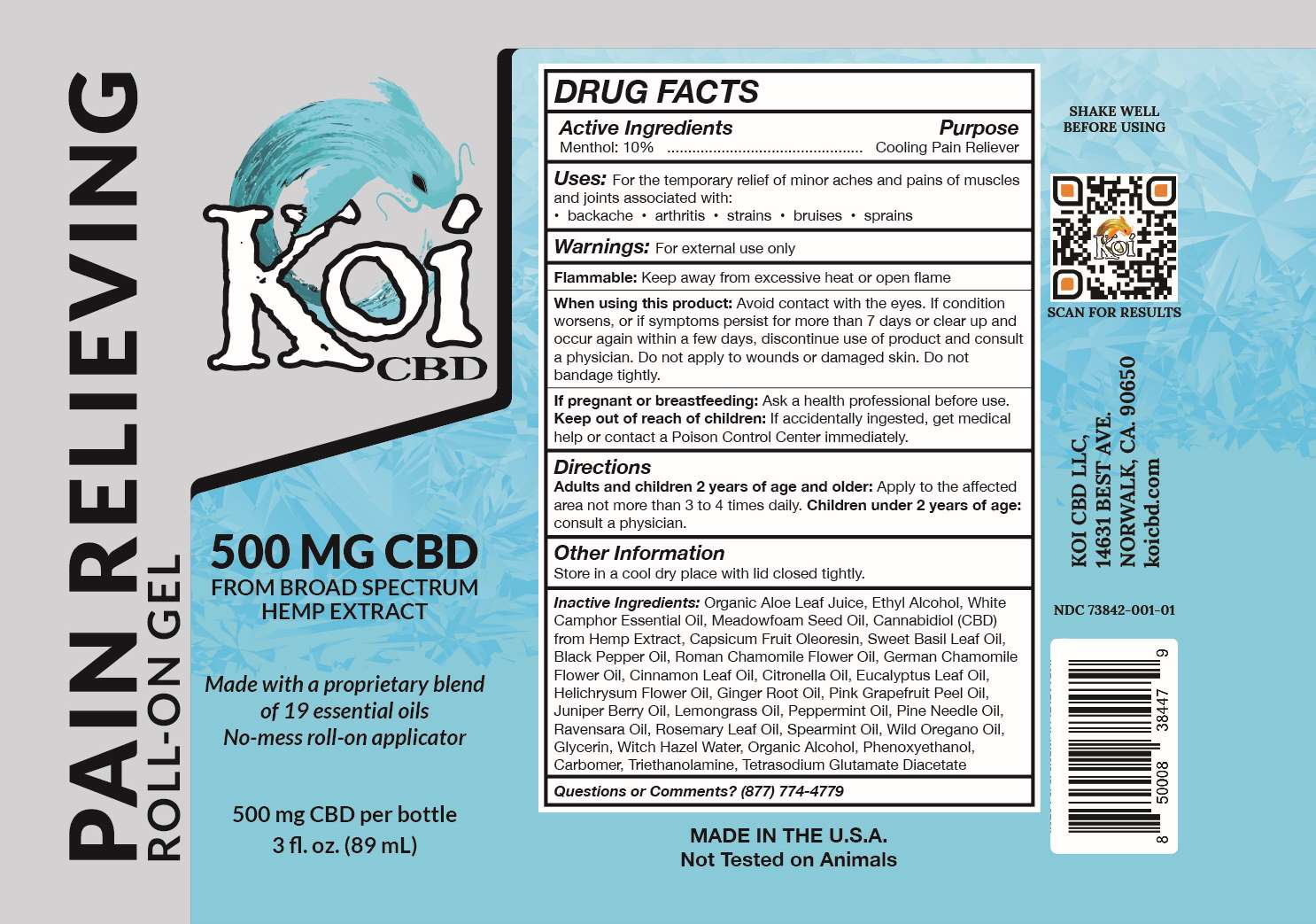 DRUG LABEL: Pain Relieving Roll-On Gel
NDC: 73842-001 | Form: GEL
Manufacturer: Koi CBD LLC
Category: otc | Type: HUMAN OTC DRUG LABEL
Date: 20200319

ACTIVE INGREDIENTS: MENTHOL 100 mg/1 mL
INACTIVE INGREDIENTS: CINNAMON LEAF OIL; CITRONELLA OIL; GRAPEFRUIT OIL; WEST INDIAN LEMONGRASS OIL; ALOE ARBORESCENS LEAF; CAMPHOR OIL, WHITE; MEADOWFOAM SEED OIL; CHAMOMILE FLOWER OIL; CAPSICUM OLEORESIN; BLACK PEPPER OIL; BASIL; TROLAMINE; TETRASODIUM GLUTAMATE DIACETATE; HELICHRYSUM ITALICUM FLOWER OIL; GINGER OIL; JUNIPER BERRY OIL; PEPPERMINT OIL; PINE NEEDLE OIL (PINUS SYLVESTRIS); CRYPTOCARYA AGATHOPHYLLA LEAF OIL; ROSEMARY OIL; SPEARMINT OIL; OREGANO LEAF OIL; CARBOMER HOMOPOLYMER, UNSPECIFIED TYPE; CANNABIS SATIVA FLOWERING TOP; GLYCERIN; PHENOXYETHANOL; WITCH HAZEL; EUCALYPTUS OIL; ALCOHOL

Koi Muscle Gel Roll-On

Pain Relieving Roll-On Gel

Active ingredient Purpose

Menthol 10%.............Cooling Pain Reliever

PURPOSE

Uses: For the temporary relief of minor aches and pains of muscles and joints associated with:

• backache • arthritis • strains • bruises • sprains

Warnings: For external use only

Flammable: Keep away from excessive heat or open flame.

When using this product: Avoid contact with the eyes. If condition worsens, or if symptoms persist for more than 7 days or clear up and occur again within a few days, discontinue use of product and consult a physician. Do not apply to wounds or damaged skin. Do not bandage tightly.

Do not use in eyes. In case of contact, rinse thoroughly with water.

Directions

Adults and children 2 years of age and older: Apply to the affected area not more than 3 to 4 times daily. Children under 2 years of age: consult a physician.

PREGNANCY OR BREAST FEEDING

If pregnant or breastfeeding: Ask a health professional before use.

Keep out of reach of children: If accidentally ingested, get medical help or contact a Poison Control Center immediately.

OTHER SAFETY INFORMATION

Store in a cool dry place with lid closed tightly.

INACTIVE INGREDIENT

Inactive Ingredients: Organic Aloe Leaf Juice, Ethyl Alcohol, White Camphor Essential Oil, Meadowfoam Seed Oil, Cannabidiol (CBD)

from Hemp Extract, Capsicum Fruit Oleoresin, Sweet Basil Leaf Oil, Black Pepper Oil, Roman Chamomile Flower Oil, German Chamomile Flower Oil, Cinnamon Leaf Oil, Citronella Oil, Eucalyptus Leaf Oil, Helichrysum Flower Oil, Ginger Root Oil, Pink Grapefruit Peel Oil, Juniper Berry Oil, Lemongrass Oil, Peppermint Oil, Pine Needle Oil, Ravensara Oil, Rosemary Leaf Oil, Spearmint Oil, Wild Oregano Oil, Glycerin, Witch Hazel Water, Organic Alcohol, Phenoxyethanol, Carbomer, Triethanolamine, Tetrasodium Glutamate Diacetate

Questions or Comments? (877) 744-4779

DOSAGE AND ADMINISTRATION

Adults and children 2 years of age and older: Apply to the affected area not more than 3 to 4 times daily. Children under 2 years of age: consult a physician.

INDICATIONS AND USAGE

Uses: For the temporary relief of minor aches and pains of muscles and joints associated with:

• backache • arthritis • strains • bruises • sprains

Individual Unit Label

NDC 73842-001-01 Roll On Bottle 89 mL

Pain Relieving Roll-On Gel 6-pack Label

NDC 73842-001-02 Case of 6 bottles (Net Vol. 534 mL)